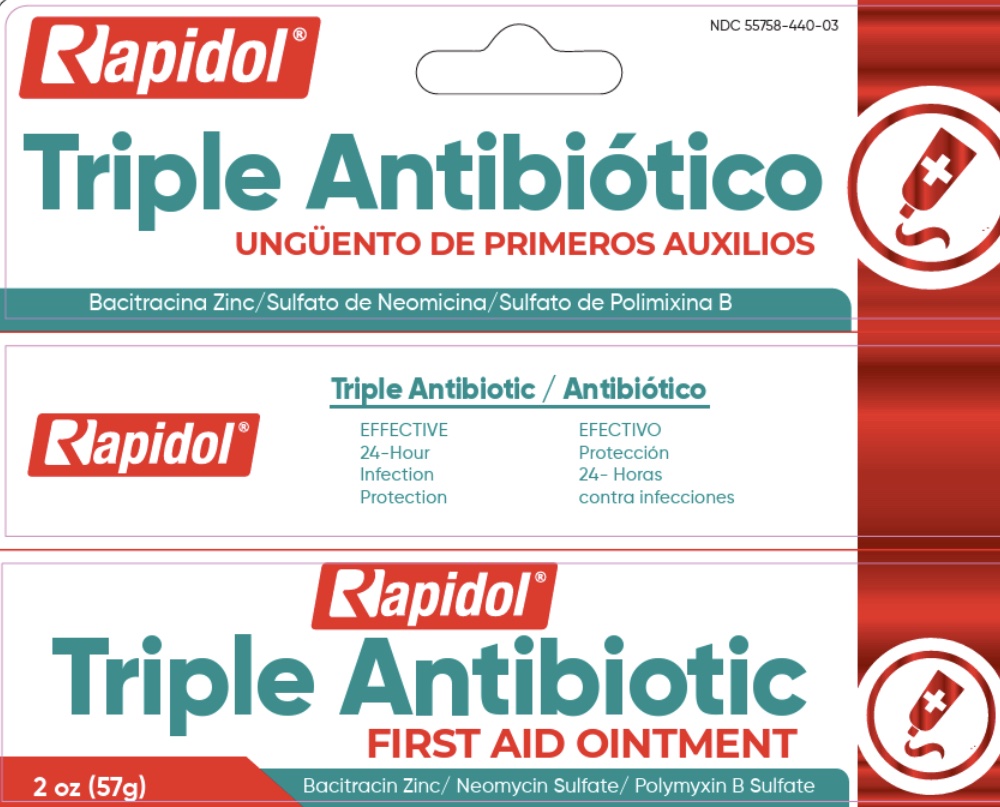 DRUG LABEL: Rapidol
NDC: 55758-440 | Form: OINTMENT
Manufacturer: Pharmadel LLC
Category: otc | Type: HUMAN OTC DRUG LABEL
Date: 20251117

ACTIVE INGREDIENTS: POLYMYXIN B SULFATE 5000 [USP'U]/1 g; BACITRACIN ZINC 400 [USP'U]/1 g; NEOMYCIN SULFATE 3.5 mg/1 g
INACTIVE INGREDIENTS: WHITE PETROLATUM

Rapidol Triple Antibiotic (DIL)

Active ingredients & Purpose

Active ingredients | Purpose
Bacitracin zinc 400 units .................. | First aid antibiotic
Neomycin sulfate 3.5 mg.................. | First aid antibiotic
Polymyxin B sulfate 5,000 units ....... | First aid antibiotic

Uses

First aid to help prevent infection in minor cuts, scrapes, and burns.

Warnings

For external use only.

Do not use

- in the eyes
- over large areas of the body
- if you are allergic to any of the ingredients

Ask a doctor before use if you have

- deep or puncture wounds
- animal bites
- serious burns

Stop use and ask a doctor if

- condition persists or gets worse
- a rash or other allergic reaction develops
- you need to use longer than 1 week

If pregnant or breast-feeding,

ask a health professional before use.

Keep out of reach of children.

If swallowed, get medical help or contact a Poison Control Center immediately.

Directions

- clean the affected area
- apply a small amount of this product (an amount equal to the surface of the tip of a finger) on the area 1 to 3 times daily
- may be covered with a sterile bandage

Other information

- store between (68-77°F) 20-25°C
- don’t use if foil seal under cap is punctured, torn, or missing

Inactive ingredients

white petrolatum